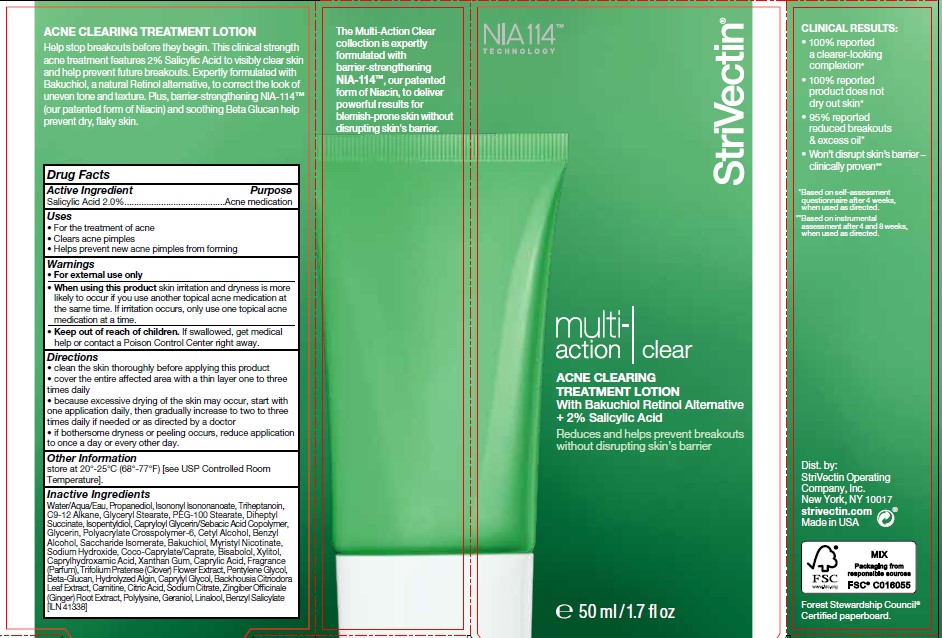 DRUG LABEL: MULTI-ACTION CLEAR - ACNE CLEARING TREATMENT
NDC: 76147-301 | Form: LOTION
Manufacturer: StriVectin Operating Company, Inc.
Category: otc | Type: HUMAN OTC DRUG LABEL
Date: 20251209

ACTIVE INGREDIENTS: SALICYLIC ACID 2 g/100 mL
INACTIVE INGREDIENTS: BAKUCHIOL; MYRISTYL NICOTINATE; SODIUM HYDROXIDE; AMMONIUM ACRYLOYLDIMETHYLTAURATE, DIMETHYLACRYLAMIDE, LAURYL METHACRYLATE AND LAURETH-4 METHACRYLATE COPOLYMER, TRIMETHYLOLPROPANE TRIACRYLATE CROSSLINKED (45000 MPA.S); ISOPENTYLDIOL; ISONONYL ISONONANOATE; LINALOOL, (+/-)-; TRIFOLIUM PRATENSE FLOWER; BACKHOUSIA CITRIODORA LEAF OIL; GINGER; SODIUM CITRATE; CITRIC ACID MONOHYDRATE; YEAST .BETA.-D-GLUCAN; CAPRYLYL GLYCOL; CARNITINE; PROPANEDIOL; GLYCERYL STEARATE/PEG-100 STEARATE; CETYL ALCOHOL; CAPRYLOYL GLYCERIN/SEBACIC ACID COPOLYMER (2000 MPA.S); GLYCERIN; CAPRYLHYDROXAMIC ACID; PENTYLENE GLYCOL; SACCHARIDE ISOMERATE; XANTHAN GUM; COCO-CAPRYLATE/CAPRATE; LEVOMENOL; XYLITOL; CAPRYLIC ACID; C9-11 ALKANE/CYCLOALKANE; DIHEPTYL SUCCINATE; WATER; POLY-L-LYSINE (30000-70000 MW); GERANIOL; BENZYL SALICYLATE; TRIHEPTANOIN

StriVectin - MULTI ACTION - CLEAR - ACNE CLEARING TREATMENT LOTION (76147-301)

ACTIVE INGREDIENTS

SALICYLIC ACID 2%

PURPOSE

ACNE MEDICATION

USES

- For the treatment of acne.
- Clears acne pimples.
- Helps prevent new acne pimples from forming.

WARNINGS

- For external use only
- When using this product skin irritation and dryness is more likely to occur if you use another topical acne medication at the same time. If irritation occurs, only use one topical acne medication at a time.

- Keep out of reach of children. If swallowed, get medical help or contact a Poison Control Center right away.

DIRECTIONS

- clean the skin thoroughly before applying this product
- cover the entire affected area with a thin layer one to three times daily
- because excessive drying of the skin may occur, start with one application daily, then gradually increase to two to three times daily if needed or as directed by a doctor
- if bothersome dryness or peeling occurs, reduce application to once a day or every other day.

OTHER INFORMATION

store at 20°-25°C (68°-77°F) [see USP Controlled Room Temperature].

INACTIVE INGREDIENTS

Water/Aqua/Eau, Propanediol, Isononyl Isononanoate, Triheptanoin, C9-12 Alkane, Glyceryl Stearate, PEG-100 Stearate, Diheptyl Succinate, Isopentyldiol, Capryloyl Glycerin/Sebacic Acid Copolymer, Glycerin, Polyacrylate Crosspolymer-6, Cetyl Alcohol, Benzyl Alcohol, Saccharide Isomerate, Bakuchiol, Myristyl Nicotinate, Sodium Hydroxide, Coco-Caprylate/Caprate, Bisabolol, Xylitol, Caprylhydroxamic Acid, Xanthan Gum, Caprylic Acid, Fragrance (Parfum), Trifolium Pratense (Clover) Flower Extract, Pentylene Glycol, Beta-Glucan, Hydrolyzed Algin, Caprylyl Glycol, Backhousia Citriodora Leaf Extract, Carnitine, Citric Acid, Sodium Citrate, Zingiber Officinale (Ginger) Root Extract, Polylysine, Geraniol, Linalool, Benzyl Salicylate [ILN 41338]